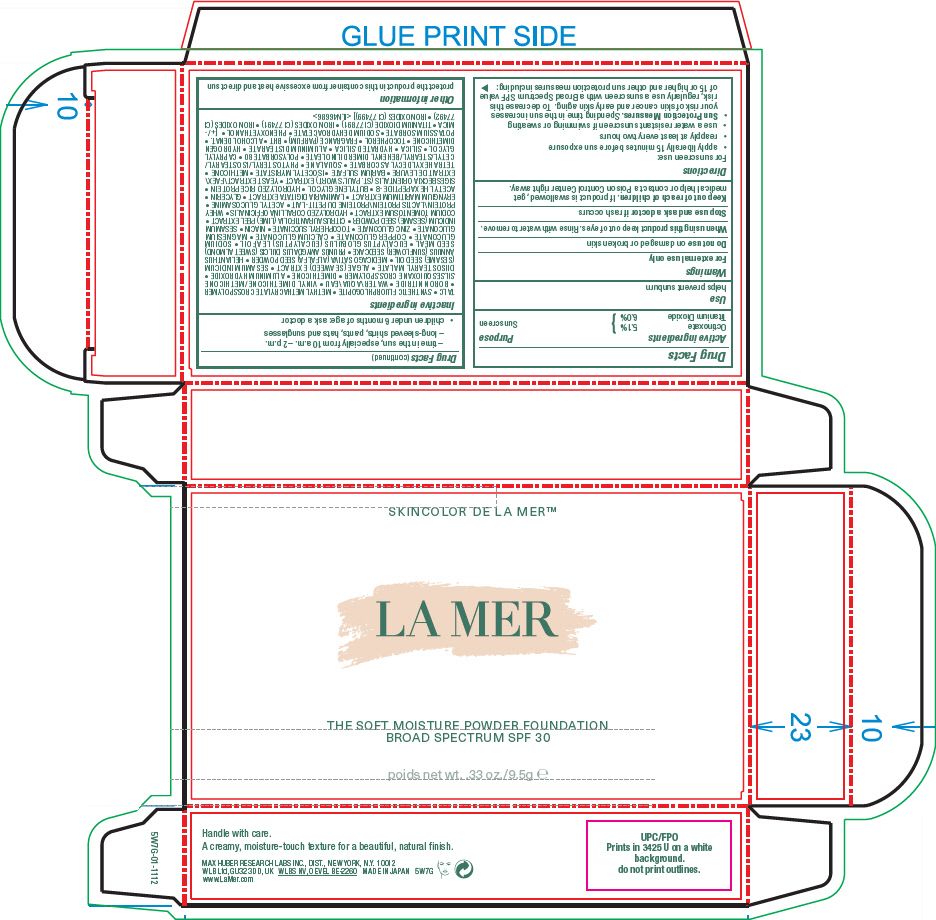 DRUG LABEL: LA MER THE SOFT MOISTURE FOUNDATION BROAD SPECTRUM SPF 30
NDC: 65966-020 | Form: POWDER
Manufacturer: MAX HUBER RESEARCH LAB INC
Category: otc | Type: HUMAN OTC DRUG LABEL
Date: 20251231

ACTIVE INGREDIENTS: OCTINOXATE 5.1 g/100 g; TITANIUM DIOXIDE 6 g/100 g
INACTIVE INGREDIENTS: TALC; METHYL METHACRYLATE/GLYCOL DIMETHACRYLATE CROSSPOLYMER; BORON NITRIDE; WATER; VINYL DIMETHICONE/METHICONE SILSESQUIOXANE CROSSPOLYMER; DIMETHICONE; ALUMINUM HYDROXIDE; DIISOSTEARYL MALATE; NORI; SESAME OIL; ALFALFA SEED; HELIANTHUS ANNUUS SEEDCAKE; EUCALYPTUS GUM; SODIUM GLUCONATE; COPPER GLUCONATE; CALCIUM GLUCONATE; MAGNESIUM GLUCONATE; ZINC GLUCONATE; .ALPHA.-TOCOPHEROL SUCCINATE, D-; NIACIN; SESAME SEED; LIME PEEL; CODIUM TOMENTOSUM; WHEY; N-ACETYLGLUCOSAMINE; LAMINARIA DIGITATA; GLYCERIN; ACETYL HEXAPEPTIDE-8; BUTYLENE GLYCOL; YEAST, UNSPECIFIED; BARIUM SULFATE; ISOCETYL MYRISTATE; METHICONE (20 CST); SQUALANE; PHYTOSTERYL/ISOSTEARYL/CETYL/STEARYL/BEHENYL DIMER DILINOLEATE; POLYSORBATE 80; SILICON DIOXIDE; HYDRATED SILICA; ALUMINUM DISTEARATE; TOCOPHEROL; HYDROGEN DIMETHICONE (13 CST); ALCOHOL; SODIUM DEHYDROACETATE; MICA; FERRIC OXIDE RED; FERRIC OXIDE YELLOW; FERROSOFERRIC OXIDE; FRAGRANCE LAVENDER & CHIA F-153480; PHENOXYETHANOL; POTASSIUM SORBATE; BUTYLATED HYDROXYTOLUENE; CAPRYLYL GLYCOL; TETRAHEXYLDECYL ASCORBATE; SIGESBECKIA ORIENTALIS FLOWERING TOP; DISINTEGRIN AND METALLOPROTEINASE DOMAIN-CONTAINING PROTEIN 11; ERYNGIUM MARITIMUM ROOT; CORALLINA OFFICINALIS; ALMOND; FLUORBENSIDE

LA MER THE SOFT MOISTURE FOUNDATION BROAD SPECTRUM SPF 30

Drug Facts

Active ingredients

Octinoxate 5.1%
Titanium Dioxide 6.0%

Purpose

Sunscreen

Use

helps prevent sunburn

Warnings

For external use only

Do not use on damaged or broken skin

When using this product keep out of eyes. Rinse with water to remove.

Stop use and ask a doctor if rash occurs

Keep out of reach of children. If product is swallowed, get medical help or contact a Poison Control Center right away.

Directions

For sunscreen use:

- apply liberally 15 minutes before sun exposure
- reapply at least every two hours
- use a water resistant sunscreen if swimming or sweating
- Sun Protection Measures. Spending time in the sun increases your risk of skin cancer and early skin aging. To decrease this risk, regularly use a sunscreen with a Broad Spectrum SPF value of 15 or higher and other sun protection measures including:
  - time in the sun, especially from 10 a.m. – 2 p.m.
  - long-sleeve shirts, pants, hats and sunglasses
- children under 6 months of age: ask a doctor

Inactive ingredients

TALC • SYNTHETIC FLUORPHLOGOPITE • METHYL METHACRYLATE CROSSPOLYMER • BORON NITRIDE • WATER\AQUA\EAU • VINYL DIMETHICONE/METHICONE SILSESQUIOXANE CROSSPOLYMER • DIMETHICONE • ALUMINUM HYDROXIDE • DIISOSTEARYL MALATE • ALGAE (SEAWEED) E X TRACT • SESAMUM INDICUM (SESAME) SEED OIL • MEDICAGO SATIVA (ALFALFA) SEED POWDER • HELIANTHUS ANNUUS (SUNFLOWER) SEEDCAKE • PRUNUS AMYGDALUS DULCIS (SWEET ALMOND) SE ED ME A L • EUCA LY PT US G LOBULUS (EUCA LY PT US) L E A F O I L • SODIUM GLUCONAT E • COPPER GLUCONAT E • CALCIUM GLUCONAT E • MAGNESIUM GLUCONATE • ZINC GLUCONATE • TOCOPHERYL SUCCINATE • NIACIN • SESAMUM INDICUM (SESAME) SEED POWDER • CITRUS AURANTIFOLIA (LIME) PEEL EXTRACT • CODIUM TOMENTOSUM EXTRACT • HYDROLYZED CORALLINA OFFICINALIS • WHEY PROTEIN\LACTIS PROTEIN\PROTEINE DU PETIT-LAIT • ACETYL GLUCOSAMINE • ERYNGIUM MARITIMUM EXTRACT • LAMINARIA DIGITATA EXTRACT • GLYCERIN • ACET YL HEXAPEPTIDE-8 • BUT YLENE GLYCOL • HYDROLYZED RICE PROTEIN • SIGESBECKIA ORIENTALIS (ST. PAUL'S WORT) EXTRACT • YEAST EXTRACT\FAEX\EXTRAIT DE LEVURE • BARIUM SULFATE • ISOCETYL MYRISTATE • METHICONE • TETRAHEXYLDECYL ASCORBATE • SQUALANE • PHYTOSTERYL/ISOSTEARYL/CETYL/STEARYL/BEHENYL DIMER DILINOLEATE • POLYSORBATE 80 • CAPRYLYL GLYCOL • SILICA • HYDRATED SILICA • ALUMINUM DISTEARATE • HYDROGEN DIMETHICONE • TOCOPHEROL • FRAGRANCE (PARFUM) • BHT • ALCOHOL DENAT. • POTASSIUM SORBATE • SODIUM DEHYDROACETATE • PHENOXYETHANOL • [+/- MICA • TITANIUM DIOXIDE (CI 77891) • IRON OXIDES (CI 77491) • IRON OXIDES (CI 77492) • IRON OXIDES (CI 77499)] <ILN46686>

Other information

protect the product in this container from excessive heat and direct sun

PRINCIPAL DISPLAY PANEL - 9.5 g Jar Carton

SKINCOLOR DE LA MER™

LA MER

THE SOFT MOISTURE POWDER FOUNDATION
BROAD SPECTRUM SPF 30

net wt. 33 oz./9.5g e